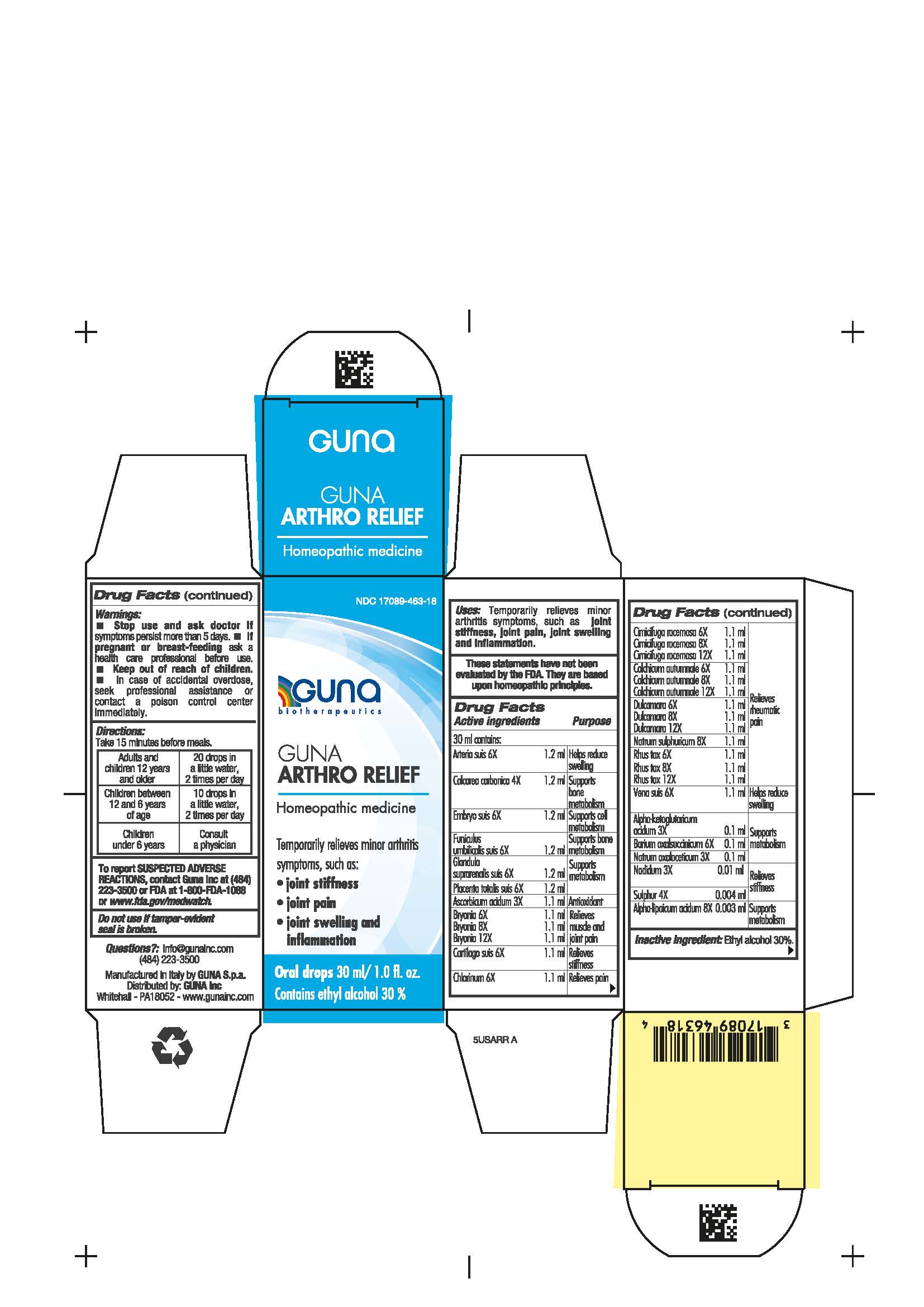 DRUG LABEL: GUNA ARTHRO RELIEF
NDC: 17089-463 | Form: SOLUTION/ DROPS
Manufacturer: Guna spa
Category: homeopathic | Type: HUMAN OTC DRUG LABEL
Date: 20201023

ACTIVE INGREDIENTS: OYSTER SHELL CALCIUM CARBONATE, CRUDE 4 [hp_X]/30 mL; SODIUM SULFATE 8 [hp_X]/30 mL; .ALPHA.-KETOGLUTARIC ACID 3 [hp_X]/30 mL; .ALPHA.-LIPOIC ACID 8 [hp_X]/30 mL; SUS SCROFA ARTERY 6 [hp_X]/30 mL; ASCORBIC ACID 3 [hp_X]/30 mL; BARIUM OXALOSUCCINATE 6 [hp_X]/30 mL; BRYONIA ALBA ROOT 6 [hp_X]/30 mL; SUS SCROFA CARTILAGE 6 [hp_X]/30 mL; CHLORINE 6 [hp_X]/30 mL; BLACK COHOSH 6 [hp_X]/30 mL; COLCHICUM AUTUMNALE BULB 6 [hp_X]/30 mL; SUS SCROFA EMBRYO 6 [hp_X]/30 mL; SOLANUM DULCAMARA FLOWER 6 [hp_X]/30 mL; SUS SCROFA UMBILICAL CORD 6 [hp_X]/30 mL; SUS SCROFA ADRENAL GLAND 6 [hp_X]/30 mL; NADIDE 3 [hp_X]/30 mL; SODIUM DIETHYL OXALACETATE 3 [hp_X]/30 mL; SUS SCROFA PLACENTA 6 [hp_X]/30 mL; TOXICODENDRON PUBESCENS LEAF 6 [hp_X]/30 mL; SULFUR 4 [hp_X]/30 mL; SUS SCROFA VEIN 6 [hp_X]/30 mL
INACTIVE INGREDIENTS: ALCOHOL 9 mL/30 mL

GUNA ARTHRO RELIEF

INDICATIONS AND USAGE

Take 15 minutes before meals

Inactive ingredient: Ethyl alcohol 30%.

QUESTIONS

info@gunainc.com
(484) 223-3500

WARNINGS

Keep out of reach of children

DIRECTIONS

Adults and children 12 years and older 20 drops in a little water 2 times per day
Children between 12 years and 6 years of age 10 drops in a little water 2 times per day
Children under 6 years consult a physician

PREGNANCY

If pregnant or breast-feeding ask a health care professional before use

WARNINGS

- Stop use and ask doctor if symptoms persist more than 5 days.
- If pregnant or breast-feeding ask a health care professional before use.
- Keep out of reach of children. In case of overdose, seek professional assistance or contact a Poison Control Center immediately.
- Contains ethyl alcohol 30%

USES

Temporarily relieves minor arthritic symptoms, such as:

- Joint stiffness
- Joint pain
- Joint swelling and inflammation

ACTIVE INGREDIENTS/PURPOSE

Arteria suis 6X Helps reduce swelling

Calcarea carbonica 4X Supports bone metabolism

Embryo suis 6X Supports cell metabolism

Funiculus umbilicalis suis 6X Supports bone metabolism

Glandula suprarenalis suis 6X Supports metabolism

Placenta totalis suis 6X Supports metabolism

Ascorbicum acidum 3X Antioxidant

Bryonia alba 6X, 8X, 12X Relieves muscle and joint pain

Cartilago suis 6X Relieves stiffness

Chlorinum 6X Relieves pain

Cimicifuga racemosa 6X, 8X, 12X Relieves rheumatic pain

Colchicum autumnale 6X, 8X, 12X Relieves rheumatic pain

Dulcamara 6X, 8X, 12X Relieves rheumatic pain

Natrum sulphuricum 8X Relieves rheumatic pain

Rhus toxicodendron 6X, 8X, 12X Relieves rheumatic pain

Vena suis 6X Helps reduce swelling

Alpha-ketoglutaricum acidum 3X Supports metabolism

Barium oxalsuccinicum 6X Supports metabolism

Natrum oxalaceticum 3X Supports metabolism

Nadidum 3X Relieves stiffness

Sulphur 4X Relieves stiffness

Alpha-lipoicum acidum 8X Supports metabolism